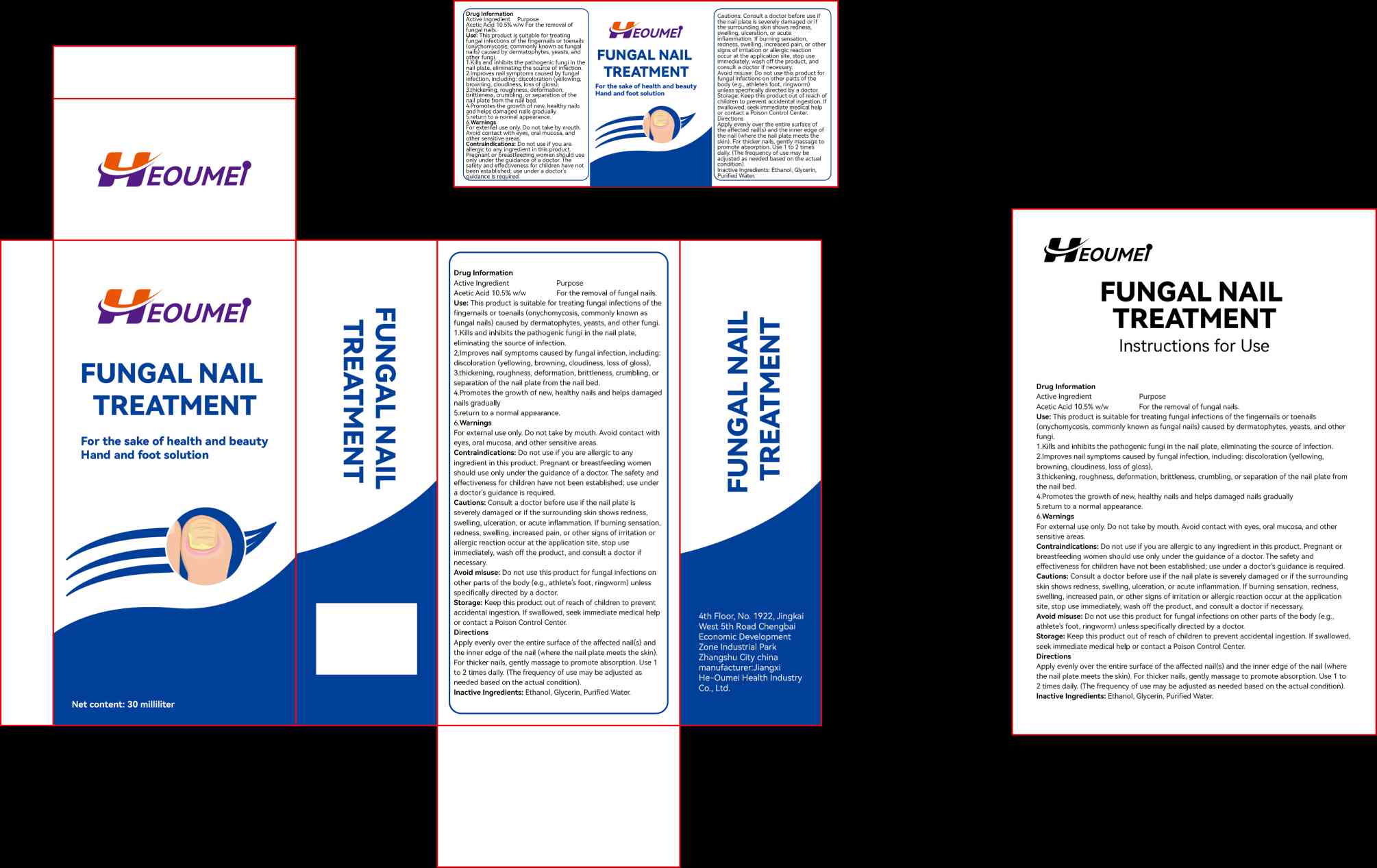 DRUG LABEL: FUNGAL NAIL TREATMENT
NDC: 87365-771 | Form: CREAM
Manufacturer: Jiangxi He-Oumei Health Industry Co., Ltd.
Category: homeopathic | Type: HUMAN OTC DRUG LABEL
Date: 20260124

ACTIVE INGREDIENTS: ACETIC ACID 1 g/1 1
INACTIVE INGREDIENTS: 2-(ETHYLSULFONYL)ETHANOL; WATER

ACTIVE INGREDIENT

Acetic Acid

PURPOSE

Treatment for toenail fungus

keep out of reach of children section

INDICATIONS AND USAGE

Treatment for toenail fungus

WARNINGS

keep out of children

DOSAGE AND ADMINISTRATION

Apply to the affected area of the nail

INACTIVE INGREDIENT

Ethanol,Glycerol,Water